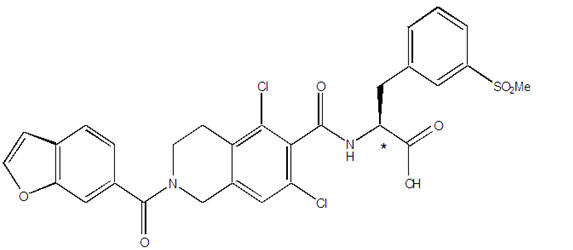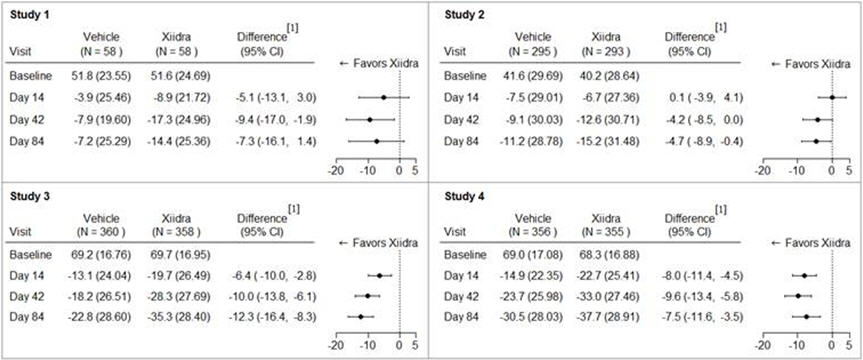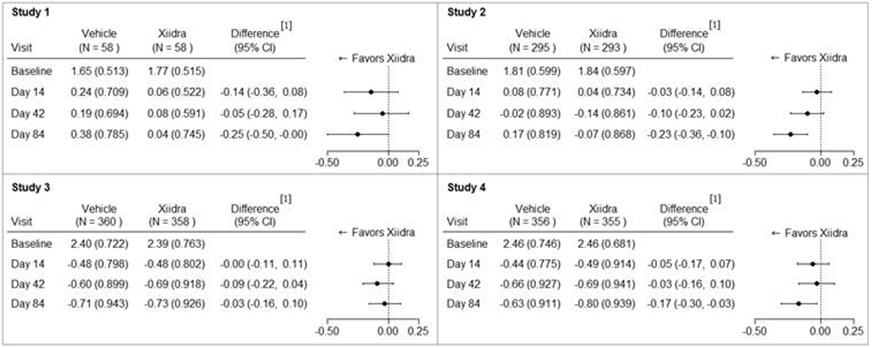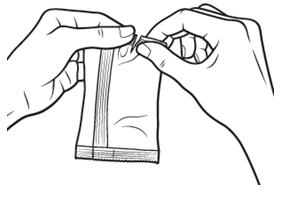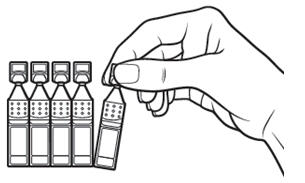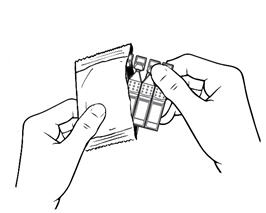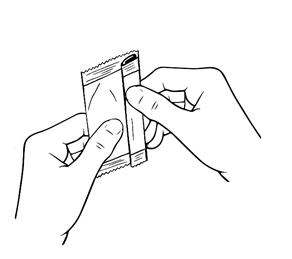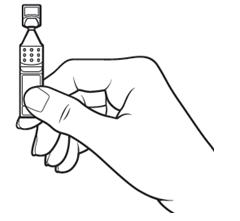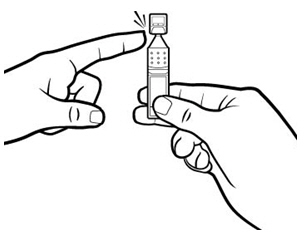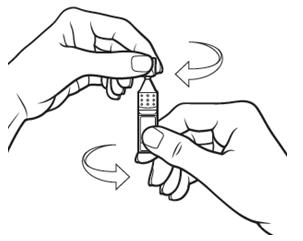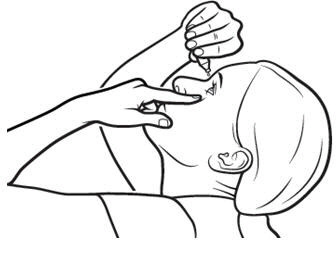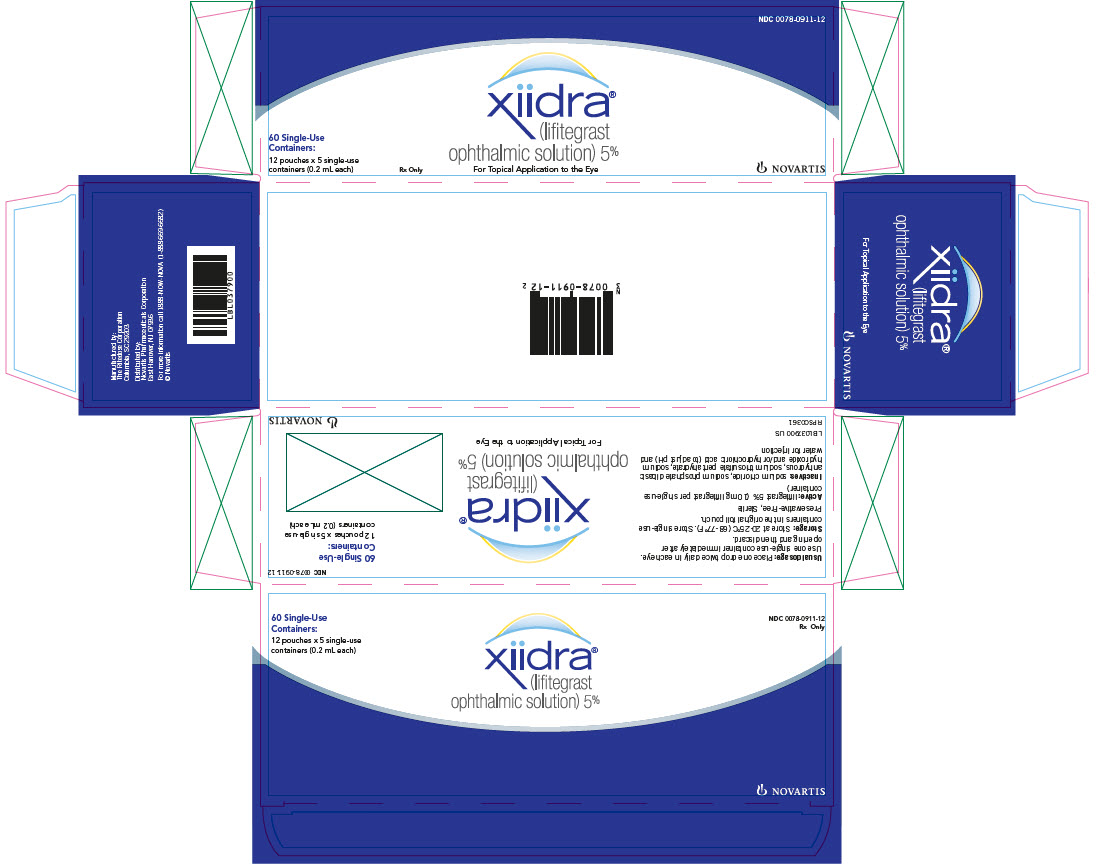 DRUG LABEL: Xiidra
NDC: 0078-0911 | Form: SOLUTION/ DROPS
Manufacturer: Novartis Pharmaceuticals Corporation
Category: prescription | Type: HUMAN PRESCRIPTION DRUG LABEL
Date: 20250818

ACTIVE INGREDIENTS: LIFITEGRAST 50 mg/1 mL
INACTIVE INGREDIENTS: SODIUM CHLORIDE; SODIUM PHOSPHATE, DIBASIC, ANHYDROUS; SODIUM THIOSULFATE; SODIUM HYDROXIDE; HYDROCHLORIC ACID; WATER

HIGHLIGHTS OF PRESCRIBING INFORMATION

These highlights do not include all the information needed to use XIIDRA safely and effectively. See full prescribing information for XIIDRA.
XIIDRA®(lifitegrast ophthalmic solution), for topical ophthalmic use
Initial U.S. Approval: 2016

1 INDICATIONS AND USAGE

Xiidra (lifitegrast ophthalmic solution) 5% is a lymphocyte function-associated antigen-1 (LFA-1) antagonist indicated for the treatment of the signs and symptoms of dry eye disease (DED). (1)

2 DOSAGE AND ADMINISTRATION

One drop twice daily in each eye (approximately 12 hours apart). (2)

3 DOSAGE FORMS AND STRENGTHS

Ophthalmic solution containing lifitegrast 50 mg/mL (5%). (3)

4 CONTRAINDICATIONS

Hypersensitivity. (4)

6 ADVERSE REACTIONS

The most common adverse reactions (incidence 5%-25%) following the use of Xiidra were instillation-site irritation, dysgeusia, and decreased visual acuity. (6)

To report SUSPECTED ADVERSE REACTIONS, contact Novartis Pharmaceuticals Corporation at 1-888-669-6682 or FDA at 1-800-FDA-1088 or www.fda.gov/medwatch.

FULL PRESCRIBING INFORMATION

1 INDICATIONS AND USAGE

Xiidra®(lifitegrast ophthalmic solution) 5% is indicated for the treatment of the signs and symptoms of dry eye disease (DED).

2 DOSAGE AND ADMINISTRATION

Instill one drop of Xiidra twice daily (approximately 12 hours apart) into each eye using a single-use container. Discard the single-use container immediately after using in each eye.

Contact lenses should be removed prior to the administration of Xiidra and may be reinserted 15 minutes following administration.

3 DOSAGE FORMS AND STRENGTHS

Ophthalmic solution containing lifitegrast 50 mg/mL (5%).

4 CONTRAINDICATIONS

Xiidra is contraindicated in patients with known hypersensitivity to lifitegrast or to any of the other ingredients in the formulation [see Adverse Reactions (6.2)].

6 ADVERSE REACTIONS

The following serious adverse reactions are described elsewhere in the labeling:

- Hypersensitivity [see Contraindications (4)]

6.1 Clinical Trials Experience

Because clinical trials are conducted under widely varying conditions, adverse reaction rates observed in clinical trials of a drug cannot be directly compared to rates in the clinical trials of another drug and may not reflect the rates observed in practice.

In five clinical trials of DED conducted with lifitegrast ophthalmic solution, 1401 patients received at least one dose of lifitegrast (1287 of which received lifitegrast 5%). The majority of patients (84%) had less than or equal to 3 months of treatment exposure. One hundred-seventy patients were exposed to lifitegrast for approximately 12 months. The majority of the treated patients were female (77%). The most common adverse reactions reported in 5%-25% of patients were instillation-site irritation, dysgeusia, and reduced visual acuity.

Other adverse reactions reported in 1%-5% of the patients were blurred vision, conjunctival hyperemia, eye irritation, headache, increased lacrimation, eye discharge, eye discomfort, eye pruritus, and sinusitis.

6.2 Postmarketing Experience

The following adverse reactions have been identified during post-approval use of Xiidra. Because these reactions are reported voluntarily from a population of uncertain size, it is not always possible to reliably estimate their frequency or establish a causal relationship to drug exposure.

Rare serious cases of hypersensitivity, including anaphylactic reaction, bronchospasm, respiratory distress, pharyngeal edema, swollen tongue, urticaria, allergic conjunctivitis, dyspnea, angioedema, and allergic dermatitis have been reported. Eye swelling and rash have also been reported [see Contraindications (4)].

8 USE IN SPECIFIC POPULATIONS

8.1 Pregnancy

Risk Summary

There are no available data on Xiidra use in pregnant women to inform any drug-associated risks. Intravenous (IV) administration of lifitegrast to pregnant rats, from premating through gestation day 17, did not produce teratogenicity at clinically relevant systemic exposures. Intravenous administration of lifitegrast to pregnant rabbits during organogenesis produced an increased incidence of omphalocele at the lowest dose tested, 3 mg/kg/day (400-fold the human plasma exposure at the recommended human ophthalmic dose [RHOD], based on the area under the curve [AUC] level). Since human systemic exposure to lifitegrast following ocular administration of Xiidra at the RHOD is low, the applicability of animal findings to the risk of Xiidra use in humans during pregnancy is unclear [see Clinical Pharmacology (12.3)].

Data

Animal Data

Lifitegrast administered daily by IV injection to rats, from premating through gestation day 17, caused an increase in mean pre-implantation loss and an increased incidence of several minor skeletal anomalies at 30 mg/kg/day, representing 5,400-fold the human plasma exposure at the RHOD of Xiidra, based on AUC. No teratogenicity was observed in the rat at 10 mg/kg/day (460-fold the human plasma exposure at the RHOD, based on AUC). In the rabbit, an increased incidence of omphalocele was observed at the lowest dose tested, 3 mg/kg/day (400-fold the human plasma exposure at the RHOD, based on AUC), when administered by IV injection daily from gestation days 7 through 19. A fetal no observed adverse effect level (NOAEL) was not identified in the rabbit.

8.2 Lactation

Risk Summary

There are no data on the presence of lifitegrast in human milk, the effects on the breastfed infant, or the effects on milk production. However, systemic exposure to lifitegrast from ocular administration is low [see Clinical Pharmacology (12.3)]. The developmental and health benefits of breastfeeding should be considered, along with the mother’s clinical need for Xiidra and any potential adverse effects on the breastfed child from Xiidra.

8.4 Pediatric Use

Safety and efficacy in pediatric patients below the age of 17 years have not been established.

8.5 Geriatric Use

No overall differences in safety or effectiveness have been observed between elderly and younger adult patients.

11 DESCRIPTION

The chemical name for lifitegrast is (S)-2-(2-(benzofuran-6-carbonyl)-5,7-dichloro-1,2,3,4-tetrahydroisoquinoline-6-carboxamido)-3-(3-(methylsulfonyl)phenyl)propanoic acid. The molecular formula of lifitegrast is C29H24Cl2N2O7S and its molecular weight is 615.5 g/mol. The structural formula of lifitegrast is:

*Chiral center

Lifitegrast is a white to off-white powder, which is soluble in water.

Xiidra (lifitegrast ophthalmic solution) 5% is a lymphocyte function-associated antigen-1 (LFA-1) antagonist supplied as a sterile, clear, colorless to slightly brownish-yellow colored, isotonic solution of lifitegrast with a pH of 7.0-8.0, and an osmolality range of 200-330 mOsmol/kg.

Xiidra contains Active:lifitegrast 50 mg/mL; Inactives: sodium chloride, sodium phosphate dibasic anhydrous, sodium thiosulfate pentahydrate, and water for injection. Sodium hydroxide and/or hydrochloric acid (to adjust pH).

12 CLINICAL PHARMACOLOGY

12.1 Mechanism of Action

Lifitegrast binds to the integrin LFA-1, a cell surface protein found on leukocytes and blocks the interaction of LFA-1 with its cognate ligand intercellular adhesion molecule-1 (ICAM-1). ICAM-1 may be overexpressed in corneal and conjunctival tissues in DED. LFA-1/ICAM-1 interaction can contribute to the formation of an immunological synapse resulting in T-cell activation and migration to target tissues. In vitrostudies demonstrated that lifitegrast may inhibit T-cell adhesion to ICAM-1 in a human T-cell line and may inhibit secretion of inflammatory cytokines in human peripheral blood mononuclear cells. The exact mechanism of action of lifitegrast in DED is not known.

12.3 Pharmacokinetics

In a subset of DED patients (n = 47) enrolled in a Phase 3 trial, the pre-dose (trough) plasma concentrations of lifitegrast were measured after 180 and 360 days of topical ocular dosing (one drop twice daily) with Xiidra (lifitegrast ophthalmic solution) 5%. A total of nine of the 47 patients (19%) had plasma lifitegrast trough concentrations above 0.5 ng/mL (the lower limit of assay quantitation). Trough plasma concentrations that could be quantitated ranged from 0.55 ng/mL to 3.74 ng/mL.

13 NONCLINICAL TOXICOLOGY

13.1 Carcinogenesis, Mutagenesis, Impairment of Fertility

Carcinogenesis

Animal studies have not been conducted to determine the carcinogenic potential of lifitegrast.

Mutagenesis

Lifitegrast was not mutagenic in the in vitroAmes assay. Lifitegrast was not clastogenic in the in vivomouse micronucleus assay. In an in vitrochromosomal aberration assay using mammalian cells (Chinese hamster ovary cells), lifitegrast was positive at the highest concentration tested, without metabolic activation.

Impairment of Fertility

Lifitegrast administered at IV doses of up to 30 mg/kg/day (5400-fold the human plasma exposure at the RHOD of lifitegrast ophthalmic solution, 5%) had no effect on fertility and reproductive performance in male and female-treated rats.

14 CLINICAL STUDIES

The safety and efficacy of lifitegrast for the treatment of DED were assessed in a total of 1181 patients (1067 of which received lifitegrast 5%) in four 12-week, randomized, multi-center, double-masked, vehicle-controlled studies. Patients were randomized to Xiidra or vehicle (placebo) in a 1:1 ratio and dosed twice a day. Use of artificial tears was not allowed during the studies. The mean age was 59 years (range, 19-97 years). The majority of patients were female (76%). Enrollment criteria included minimal signs (i.e., Corneal Fluorescein Staining and non-anesthetized Schirmer Tear Test) and symptoms (i.e., Eye Dryness Score (EDS) and Ocular Discomfort Score) severity scores at baseline.

Effects on Symptoms of Dry Eye Disease

Eye dryness score was rated by patients using a visual analogue scale (0 = no discomfort, 100 = maximal discomfort) at each study visit. The average baseline EDS was between 40 and 70. A larger reduction in EDS favoring Xiidra was observed in all studies at Day 42 and Day 84 (see Figure 1).

Figure 1: Mean Change (SD) From Baseline and Treatment Difference (Xiidra – Vehicle) in Eye Dryness Score in 12-Week Studies in Patients With Dry Eye Disease

[1] Based on analysis of covariance (ANCOVA) model adjusted for baseline value in Study 1, and ANCOVA model adjusted for baseline value and randomization stratification factors in Studies 2-4. All randomized and treated patients were included in the analysis and missing data were imputed using last-available data. In Study 1, one Xiidra-treated subject who did not have a baseline value was excluded from analysis.

Effects on Signs of Dry Eye Disease

Inferior fluorescein corneal staining score (ICSS) (0 = no staining, 1 = few/rare punctate lesions, 2 = discrete and countable lesions, 3 = lesions too numerous to count but not coalescent, 4 = coalescent) was recorded at each study visit. The average baseline ICSS was approximately 1.8 in Studies 1 and 2, and 2.4 in Studies 3 and 4. At Day 84, a larger reduction in ICSS favoring Xiidra was observed in three of the four studies (see Figure 2).

Figure 2: Mean Change (SD) From Baseline and Treatment Difference (Xiidra – Vehicle) in Inferior Corneal Staining Score in 12-Week Studies in Patients With Dry Eye Disease

[1] Based on ANCOVA model adjusted for baseline value in Study 1, and ANCOVA model adjusted for baseline value and randomization stratification factors in Studies 2-4. All randomized and treated patients were included in the analysis and missing data were imputed using last-available data. In Study 2, one vehicle-treated subject who did not have a study eye designated was excluded from analysis.

16 HOW SUPPLIED/STORAGE AND HANDLING

Xiidra (lifitegrast ophthalmic solution) 5% (50 mg/mL) is supplied in a foil pouch containing 5 low-density polyethylene 0.2 mL single-use containers.

Carton of 60 single-use containers NDC 0078-0911-12

Storage:

Store at 20°C to 25°C (68°F to 77°F). Store single-use containers in the original foil pouch.

17 PATIENT COUNSELING INFORMATION

Advise patients to read the FDA-approved patient labeling (Patient Information and Instructions for Use).

Handling the Single-use Container

Advise patients not to touch the tip of the single-use container to their eye or to any surface, in order to avoid eye injury or contamination of the solution.

Use With Contact Lenses

Advise patients that contact lenses should be removed prior to administration of Xiidra and can be reinserted 15 minutes after administration [see Dosage and Administration (2)].

Administration

Advise patients that the solution from one single-use container is to be used immediately after opening. It can be used to dose both eyes. The single-use container, including any remaining contents should be discarded immediately after administration [see Dosage and Administration (2)].

Storage Information

Instruct patients to store single-use containers in the original foil pouch until ready to use [see How Supplied/Storage and Handling (16)].

Distributed by:
Novartis Pharmaceuticals Corporation
One Health Plaza
East Hanover, NJ 07936

T2020-87

PATIENT INFORMATION
XIIDRA®(ZYE-druh)
(lifitegrast ophthalmic solution) 5%
for topical ophthalmic use

What is Xiidra?
Xiidra is a prescription eye drop solution used to treat the signs and symptoms of dry eye disease (DED). It is not known if Xiidra is safe and effective in children under 17 years of age.

Do not use Xiidra:

- If you are allergic to lifitegrast or any of the other ingredients in Xiidra, see “What are the ingredients in Xiidra?”

Before you use Xiidra, tell your doctor if you:

- are using any other eye drops
- wear contact lenses
- are pregnant or plan to become pregnant. It is not known if Xiidra will harm your unborn baby.
- are breastfeeding or plan to breastfeed. It is not known if Xiidra passes into your breast milk. Talk to your doctor about the best way to feed your baby if you use Xiidra.

How should I use Xiidra?
See the complete Instructions for Use at the end of this Patient Information leaflet for detailed instructions about the right way to use Xiidra.

- Use Xiidra as your doctor tells you.
- Use one drop of Xiidra in each eye, two times each day, about 12 hours apart.
- Use Xiidra right away after opening. Throw away the single-use container and any unused solution after you have applied the dose to both eyes. Do not save any unused Xiidra for later.

What are the possible side effects of Xiidra?
The most common side effects of Xiidra include eye irritation, discomfort, or blurred vision when the drops are applied to the eyes, and an unusual taste sensation (dysgeusia).
Seek medical care immediately if you get any symptoms of wheezing, difficulty breathing, or swollen tongue.
These are not all the possible side effects of Xiidra.
Tell your doctor if you have any side effects that bother you. You may report side effects to FDA at 1-800-FDA-1088.

How should I store Xiidra?

- Store Xiidra at room temperature between 68°F to 77°F (20°C to 25°C).
- Store Xiidra in the original foil pouch to protect it from light.
- Do not open the Xiidra foil pouch until you are ready to use the eye drops.
- Return unused single-use containers to their original foil pouch to protect from excessive light exposure.

Keep Xiidra and all medicines out of the reach of children.

General information about the safe and effective use of Xiidra.
Medicines are sometimes prescribed for purposes other than those listed in a Patient Information leaflet. You can ask your pharmacist or doctor for information about Xiidra that is written for health professionals. Do not use Xiidra for a condition for which it was not prescribed. Do not give Xiidra to other people, even if they have the same symptoms you have. It may harm them.

What are the ingredients in Xiidra?
Active ingredient: lifitegrast
Inactive ingredients: sodium chloride, sodium phosphate dibasic anhydrous, sodium thiosulfate pentahydrate, and water for injection. Sodium hydroxide and/or hydrochloric acid (to adjust pH).

Distributed by: Novartis Pharmaceuticals Corporation, One Health Plaza, East Hanover, NJ 07936
For more information, go to www.Xiidra.com or call 1-888-NOW-NOVA.

This Patient Information has been approved by the U.S. Food and Drug Administration.

Revised: June 2020

T2020-88

INSTRUCTIONS FOR USE
XIIDRA®[ZYE-druh]
(lifitegrast ophthalmic solution) 5%
for topical ophthalmic use

1. Read this Instructions for Use before you start using Xiidra and each time you get a refill. There may be new information. This leaflet does not take the place of talking to your doctor about your medical condition or your treatment.

Important Information You Need to Know Before Using Xiidra:

- Xiidra is for use in the eye.
- Wash your hands before each use to make sure you do not infect your eyes while using Xiidra.
- If you wear contact lenses, remove them before using Xiidra.
- Xiidra single-use containers are packaged in a foil pouch. Do not remove from the foil pouch until you are ready to use Xiidra.
- Do not let the tip of the Xiidra single-use container touch your eye or any other surfaces.
- Use one drop of Xiidra in each eye two times each day (one drop in the morning and one drop in the evening, approximately 12 hours apart). Each single-use container of Xiidra will give you enough medicine to treat both of your eyes, one time. There is some extra Xiidra in each single-use container in case you miss getting a drop into your eye. After you have applied the drops, throw away the single-use container and any unused Xiidra. Do not save any unused Xiidra.

Follow Steps 1 to 9 each time you use Xiidra.

Step 1.Take a foil pouch out of the Xiidra box. Open the pouch and remove the strip of single-use containers (see Figure A).

Figure A

- Pull off one single-use container from the strip (see Figure B).

Figure B

Step 2.Put the remaining strip of single-use containers back in the pouch (see Figure C).

Figure C

- Fold the edge to close the pouch (see Figure D).

Figure D

Step 3.Hold the Xiidra container upright (see Figure E).

Figure E

- Tap the top of the container until all of the solution is in the bottom part of the container (see Figure F).

Figure F

Step 4.Open the Xiidra single-use container by twisting off the tab. Make sure that the tip of the single-use container does not touch anything, to avoid contamination (see Figure G).

Figure G

Step 5.Tilt your head backwards. If you are not able to tilt your head, lie down.

Step 6.Gently pull your lower eyelid downwards and look up.

Step 7.Place the tip of the Xiidra single-use container close to your eye, but be careful not to touch your eye with it.

Step 8.Gently squeeze the single-use container and let one drop of Xiidra fall into the space between your lower eyelid and your eye. If a drop misses your eye, try again (see Figure H).

Figure H

Step 9. Repeat Steps 5 to 8for your other eye. There is enough Xiidra in one single-use container for both eyes.

- Once you have applied a drop to both eyes, throw away the opened single-use container with any remaining solution.
- If you use contact lenses, wait for at least 15 minutes before placing them back in your eyes.

Distributed by: Novartis Pharmaceuticals Corporation, One Health Plaza, East Hanover, NJ 07936

This Instructions for Use has been approved by the U.S. Food and Drug Administration.

Revised: June 2020

T2020-89

PRINCIPAL DISPLAY PANEL

NDC 0078-0911-12

Rx Only

60 Single-Use
Containers:
12 pouches x 5 single-use
containers (0.2 mL each)

xiidra®
(lifitegrast
ophthalmic solution) 5%

NOVARTIS